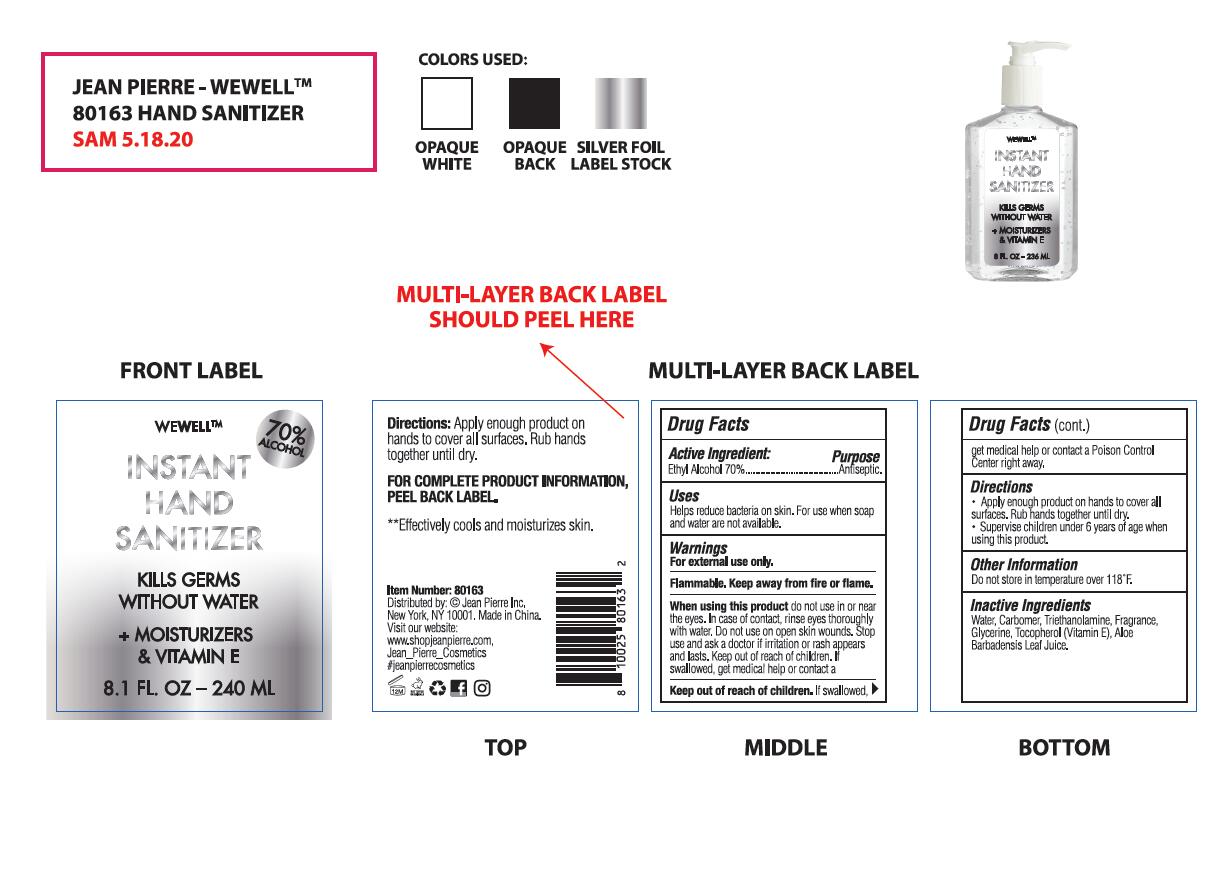 DRUG LABEL: INSTANT HAND SANITIZER
NDC: 72922-055 | Form: GEL
Manufacturer: ShangRao chunyu Technology CO.,LTD.
Category: otc | Type: HUMAN OTC DRUG LABEL
Date: 20210411

ACTIVE INGREDIENTS: ALCOHOL 70 mL/100 mL
INACTIVE INGREDIENTS: CARBOMER HOMOPOLYMER, UNSPECIFIED TYPE; TROLAMINE; WATER; GLYCERIN; ALOE VERA LEAF; PODOPHYLLUM RESIN; TOCOPHEROL

72922-055
INSTANT HAND SANITIZER

Active Ingredient(s)

Ethyl Alcohol 70%

Purpose

Antiseptic

Use

Helps reduce bacteria on skin. For use when soap and water are not available.

Warnings

For external use only. Flammable. Keep away from fire or flame.

do not use in or near tile eyes

When using this product do not use in or near tile eyes. In case of contact, rinse eyes thoroughly with water. Do not use on open skin wounds. Stop use and ask a doctor if irritation or rash appears and lasts. Keep out of reach of children. If swallowed, get medical help or contact a Poison Control Center right away.

Stop use and ask a doctor if irritation or rash appears and lasts.

Keep out of reach of children.

Directions

Apply enough product on hands to cover all surfaces. Rub hands together until dry.
Supervise children under 6 years of age when using this product.

Other information

Do not store in temperature over 118°F.

INACTIVE INGREDIENT

Water, Carbomer, Triethanolamine, Fragrance, Glycerine, Tocopherol (Vitamin E), Aloe Barbadensis Leaf Juice